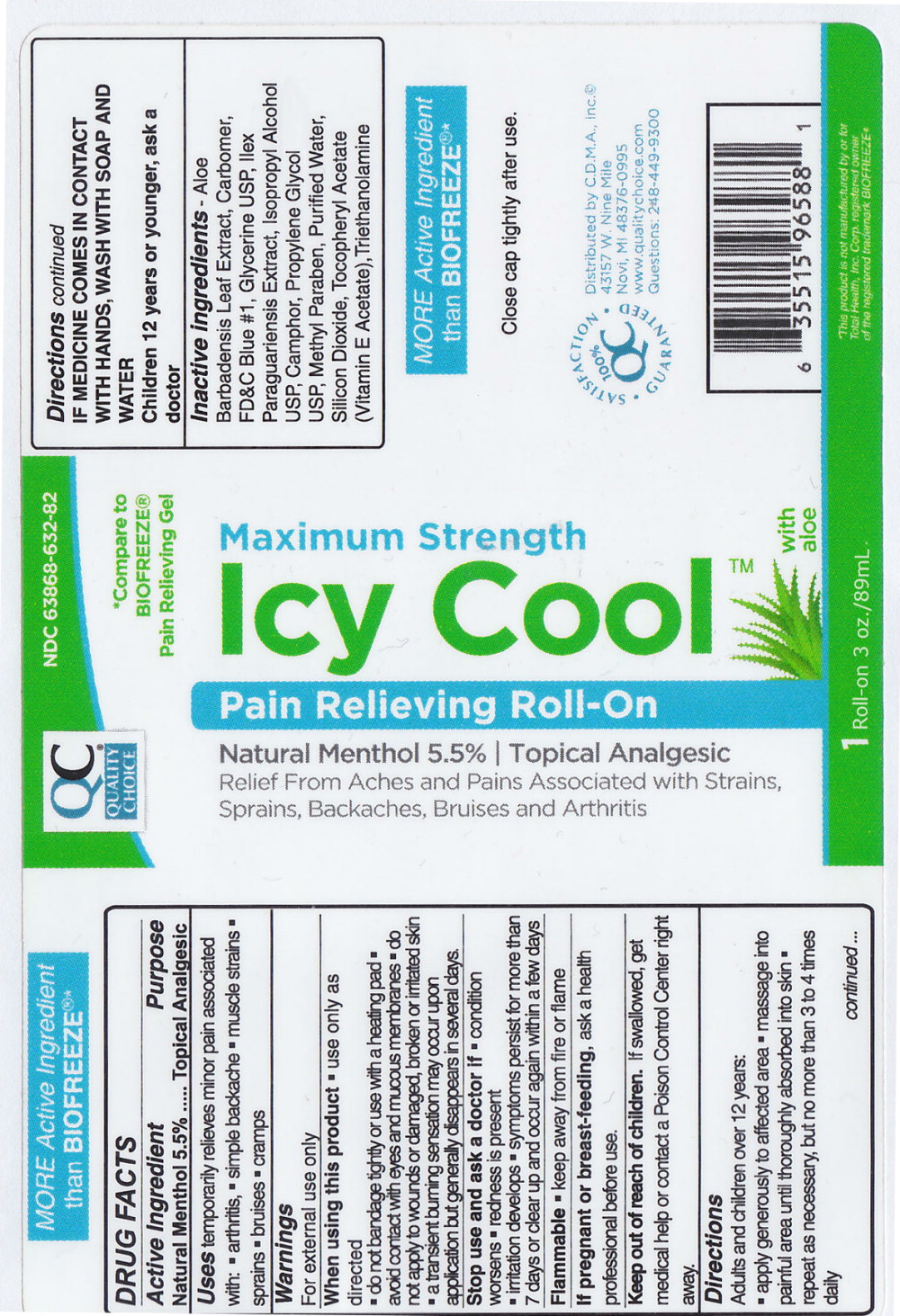 DRUG LABEL: Icy Cool 
NDC: 63868-632 | Form: GEL
Manufacturer: C.D.M.A. Inc.
Category: otc | Type: HUMAN OTC DRUG LABEL
Date: 20140814

ACTIVE INGREDIENTS: Menthol 55 mg/1 mL
INACTIVE INGREDIENTS: ALOE VERA LEAF; .ALPHA.-TOCOPHEROL ACETATE; CAMPHOR (SYNTHETIC); CARBOMER HOMOPOLYMER TYPE C (ALLYL PENTAERYTHRITOL CROSSLINKED); FD&C BLUE NO. 1; GLYCERIN; ILEX PARAGUARIENSIS LEAF; ISOPROPYL ALCOHOL; METHYLPARABEN; PROPYLENE GLYCOL; SILICON DIOXIDE; TROLAMINE; WATER

DRUG FACTS

Active Ingredient

Natural Menthol 5.5%

Purpose

Topical Analgesic

Uses

temporarily relieves minor pain associated with:

- arthritis,
- simple backache
- muscle strains
- sprains
- bruises
- cramps

Warnings

For external use only

When using this product

- use only as directed
- do not bandage tightly or use with a heating pad
- avoid contact with eyes and mucous membranes
- do not apply to wounds or damaged, broken or irritated skin
- a transient burning sensation may occur upon application but generally disappears in several days.

Stop use and ask a doctor if

- condition worsens
- redness is present
- irritation develops
- symptoms persist for more than 7 days or clear up and occur again within a few days

Flammable

- keep away from fire of flame

PREGNANCY OR BREAST FEEDING

If pregnant or breast-feeding, ask a health professional before use.

Keep out of reach of children. If swallowed, get medical help of contact a Poison Control Center right away.

Directions

Adults and children over 12 years:

- apply generously to affected area
- message into painful area until thoroughly absorbed into skin
- repeat as necessary, but no more than 3 to 4 times daily

IF MEDICINE COMES IN CONTACT WITH HANDS, WASH WITH SOAP AND WATER

Children 12 years or younger, ask a doctor

Inactive ingredients –

Aloe Barbadensis Leaf Extract, Carbomer, FD&C Blue #1, Glycerine USP, Ilex Paraguariensis Extract, Isopropyl Alcohol USP, Camphor, Propylene Glycol USP, Methyl Paraben, Purified Water, Silicon Dioxide, Tocopheryl Acetate (Vitamin E Acetate), Triethanolamine

Principal Display Panel - 3 oz. Roll on Label

QC Quality Choice

NDC 63868-632-82

*Compare to BIOFREEZE®
Pain Relieving Gel

Maximum Strength

Icy Cool TM with aloe

Pain Relieving Roll-On

Natural Menthol 5.5% | Topical Analgesic

Relief From Aches and Pains Associated with Strains, Sprains, Backaches, Bruises and Arthritis

1 Roll-on 3oz./89mL.